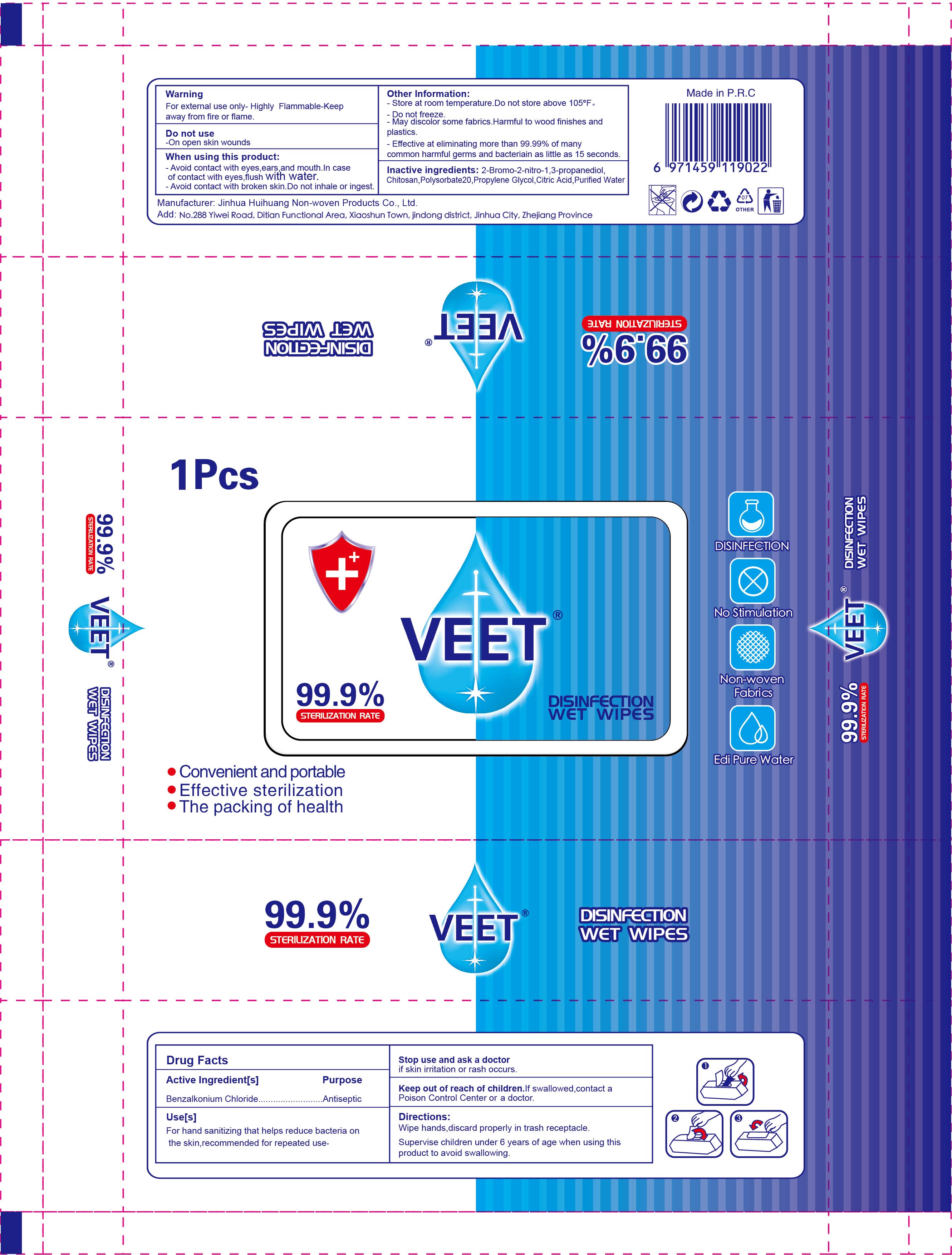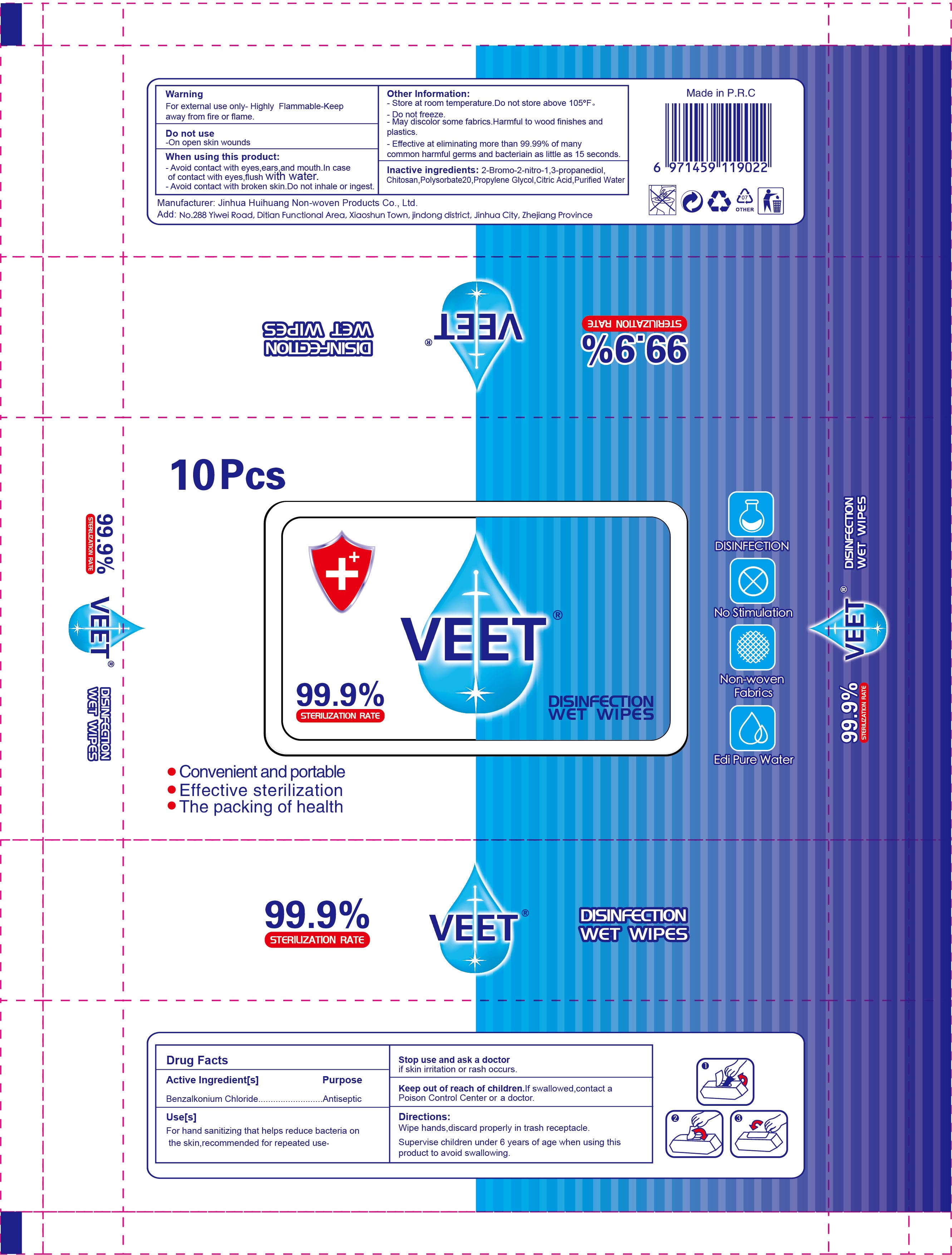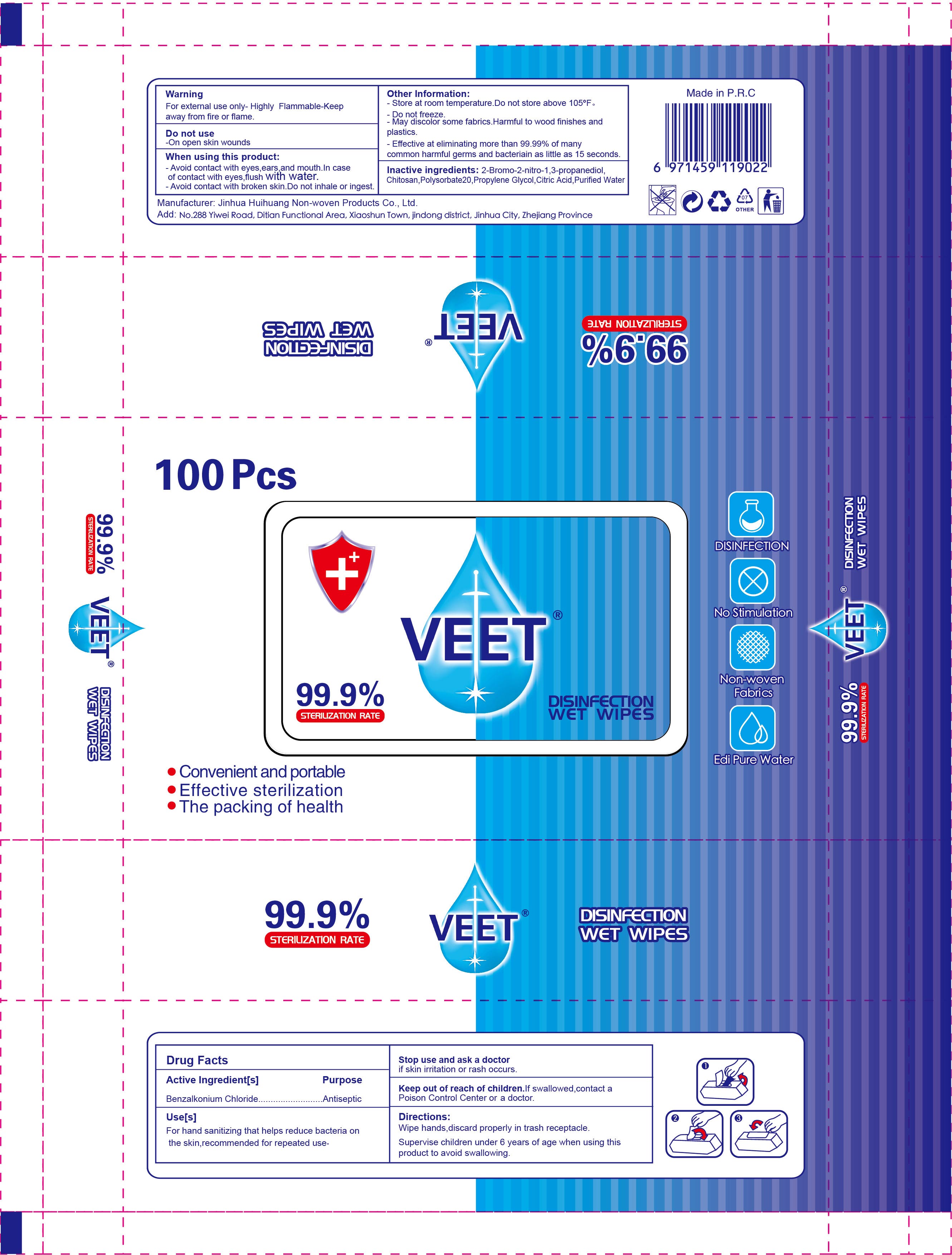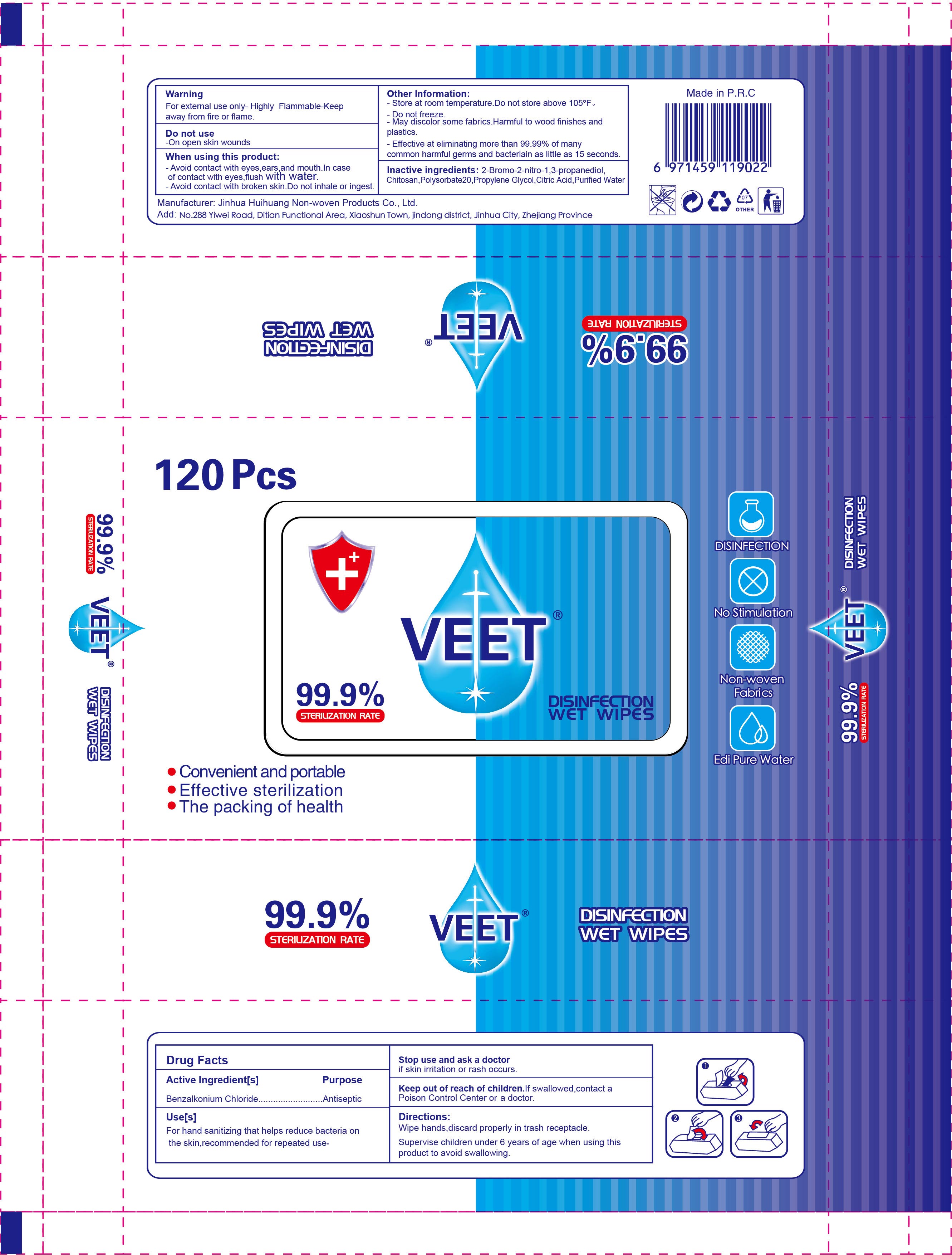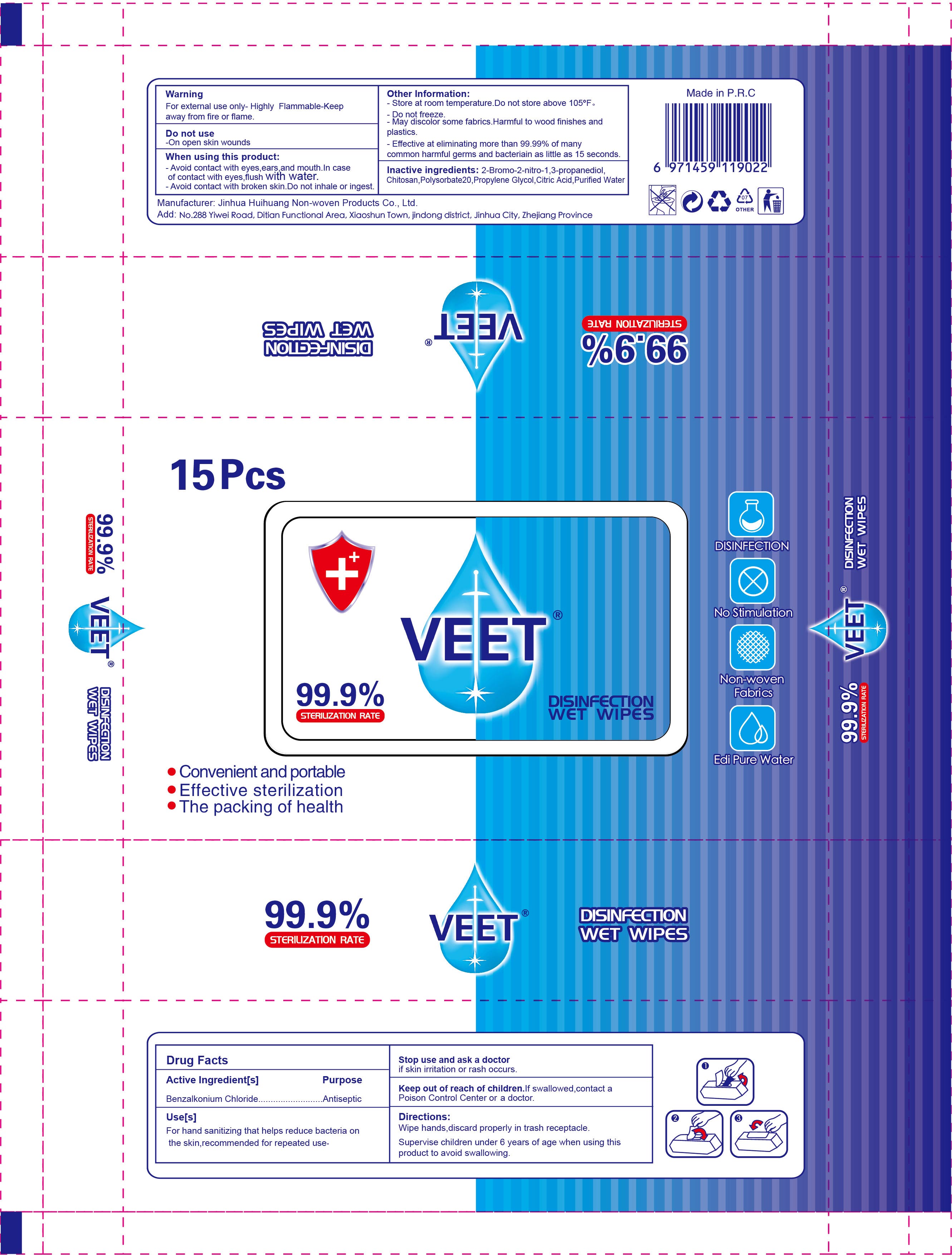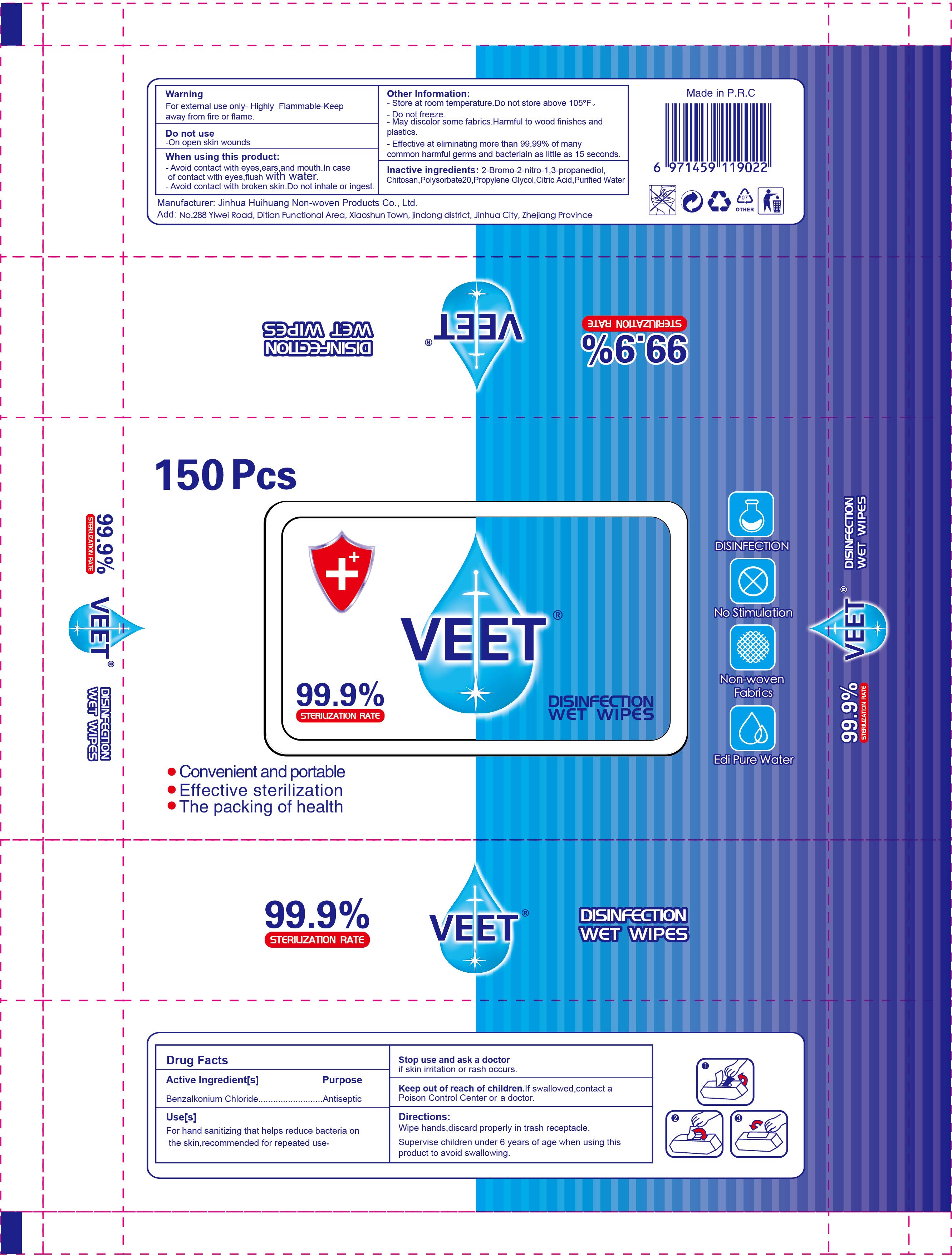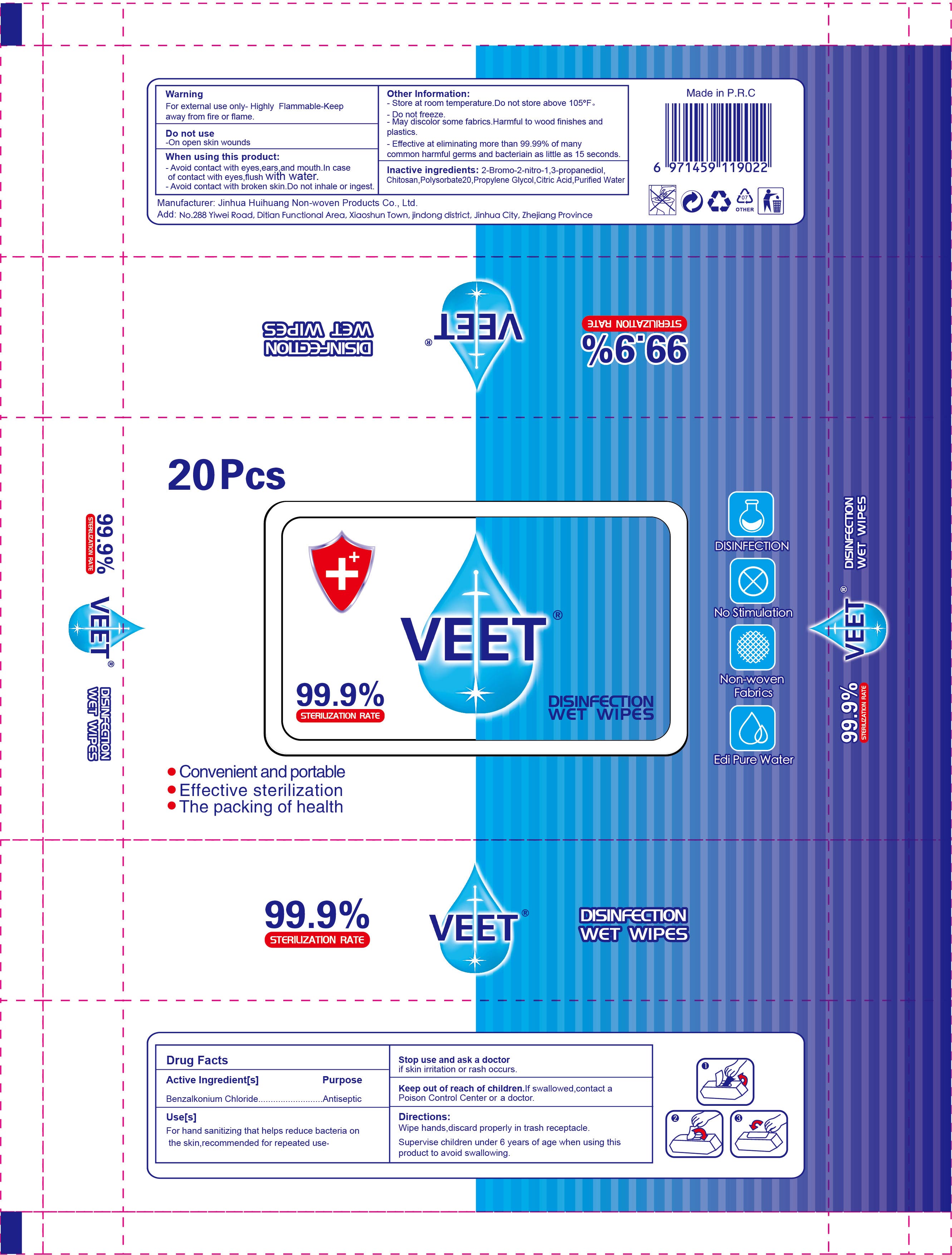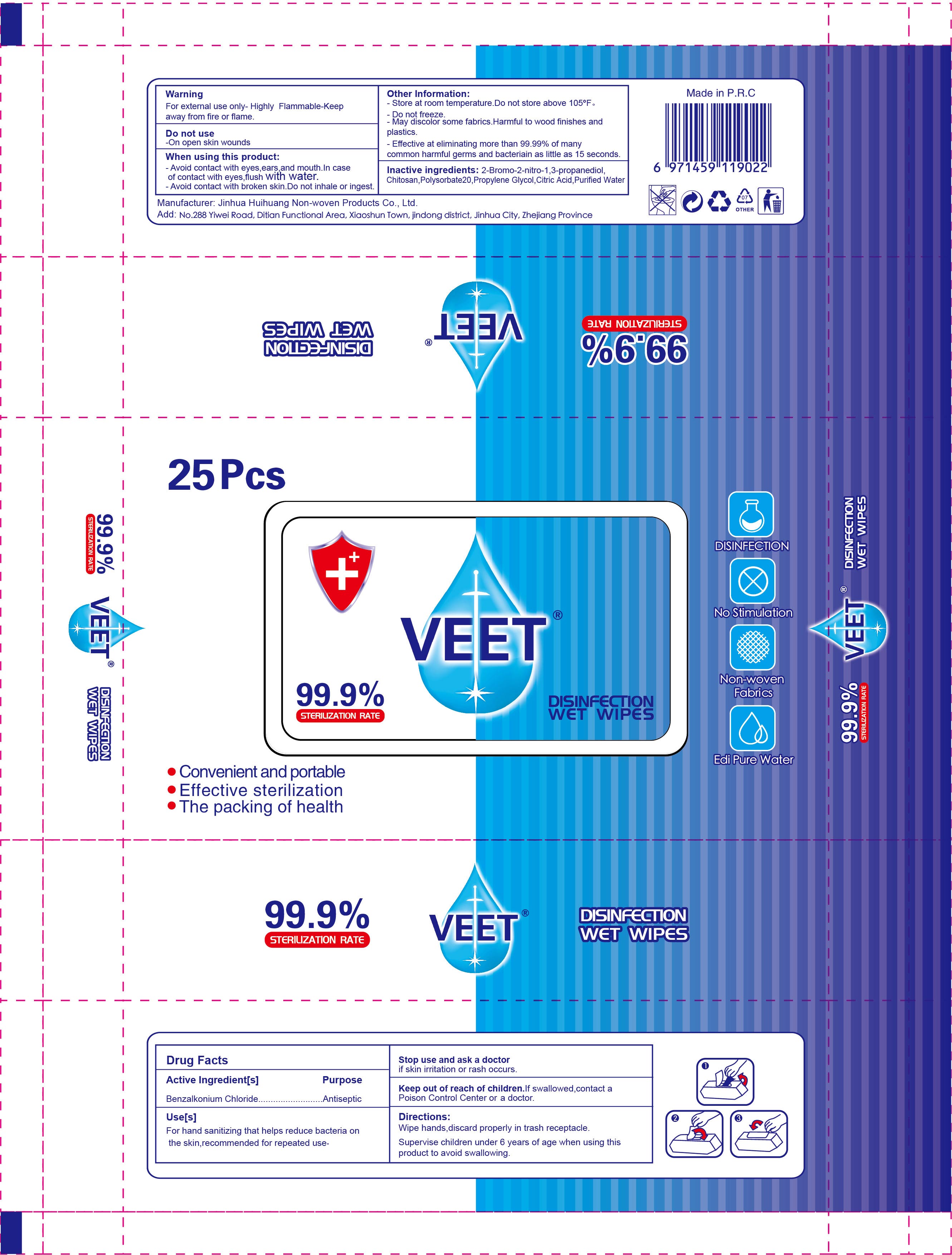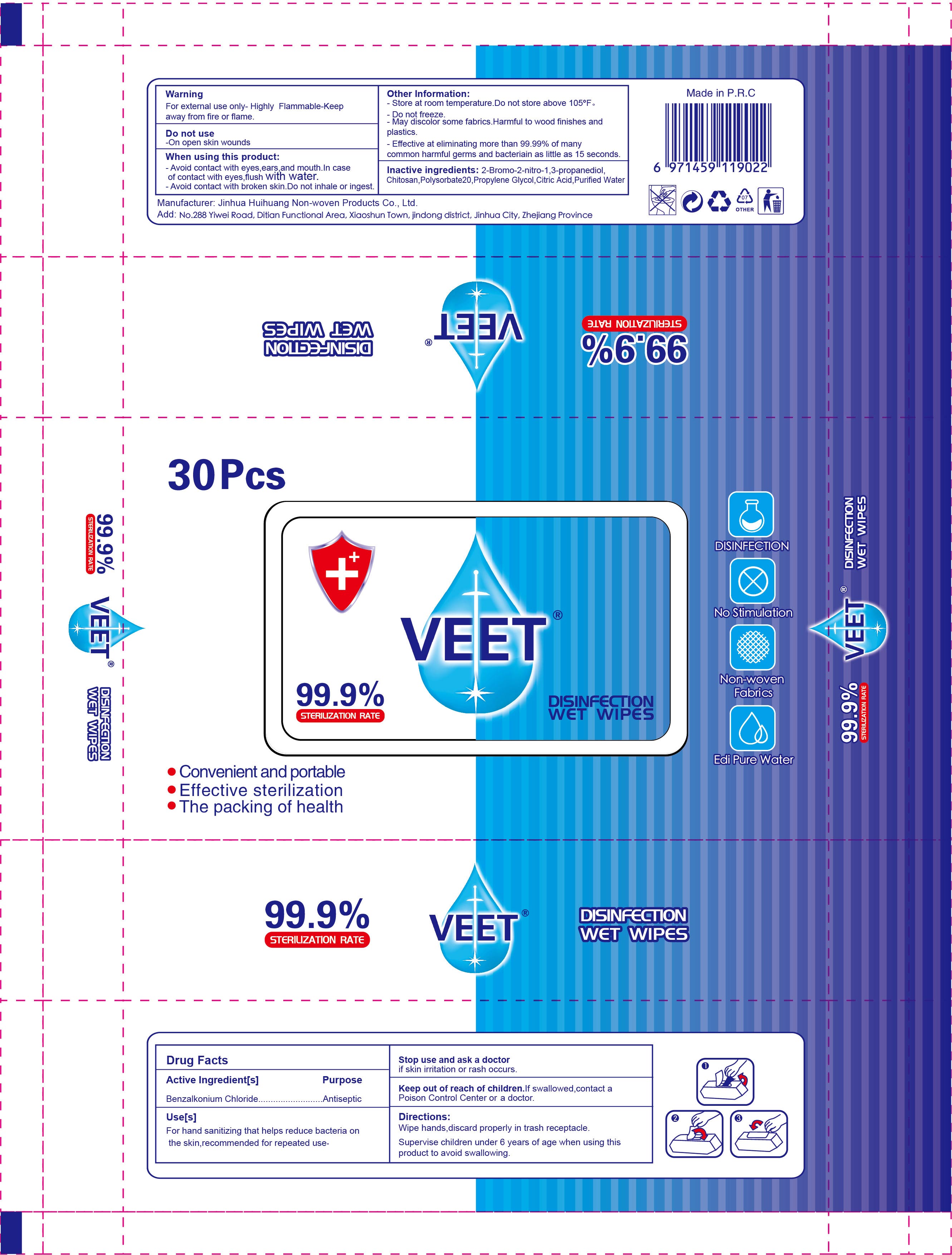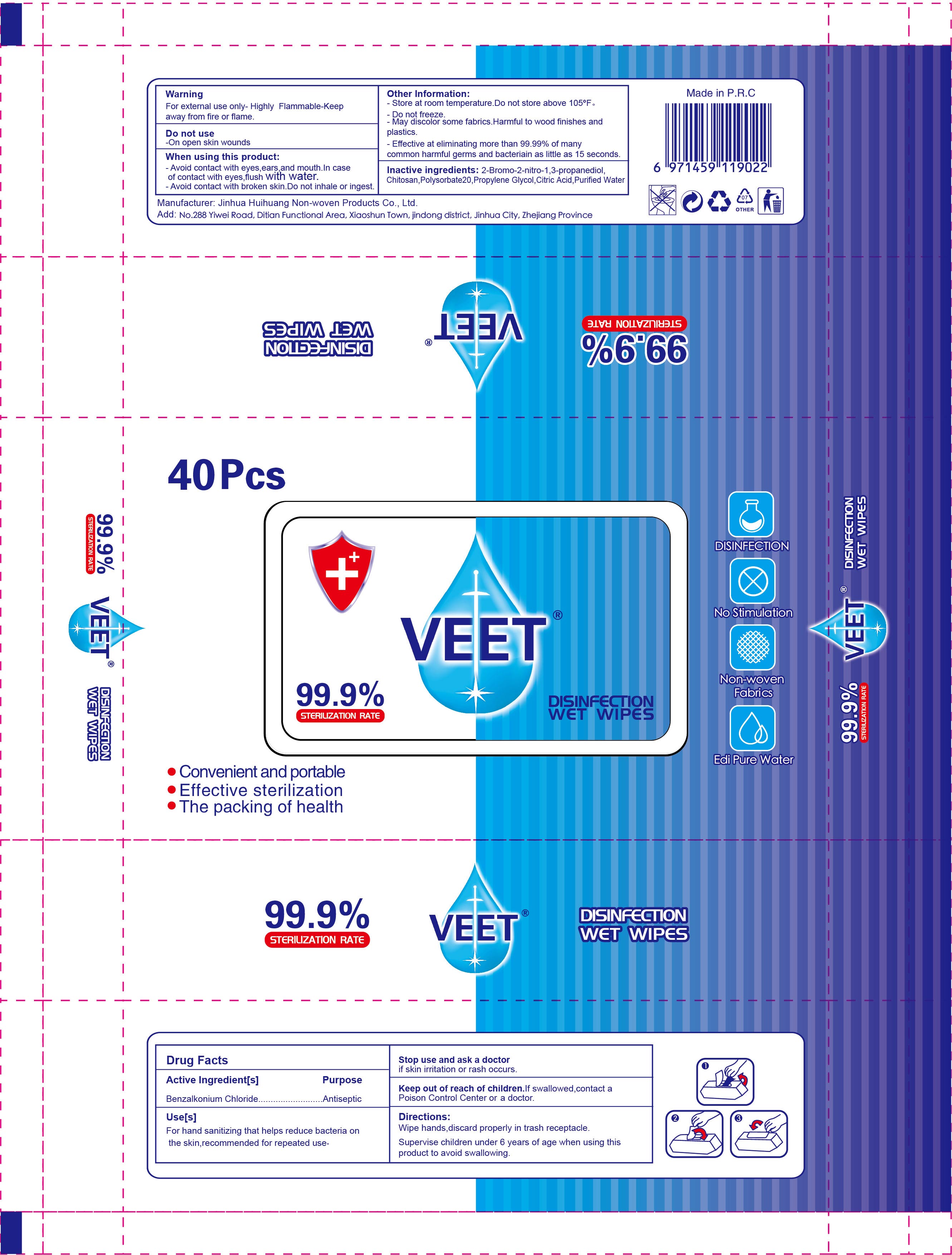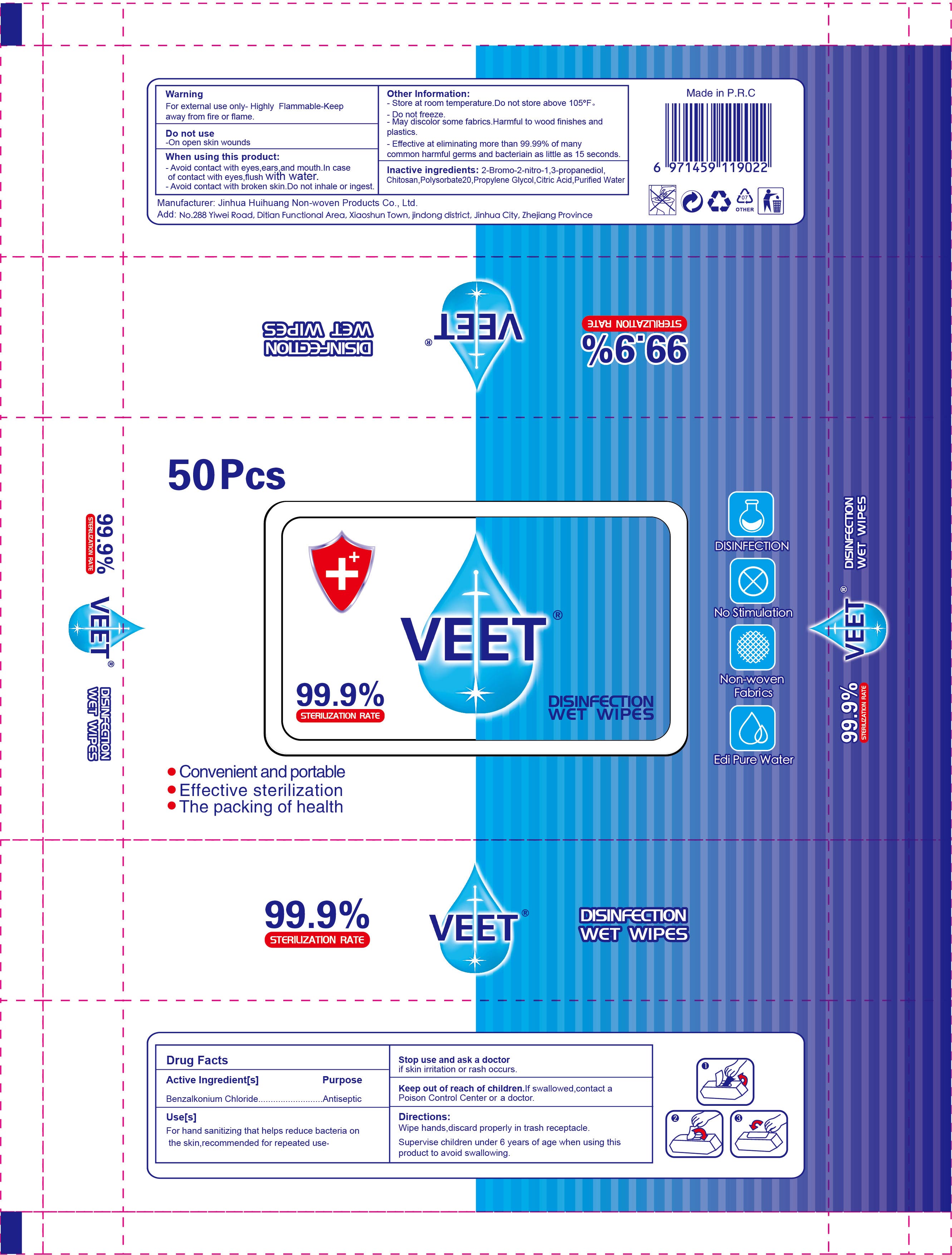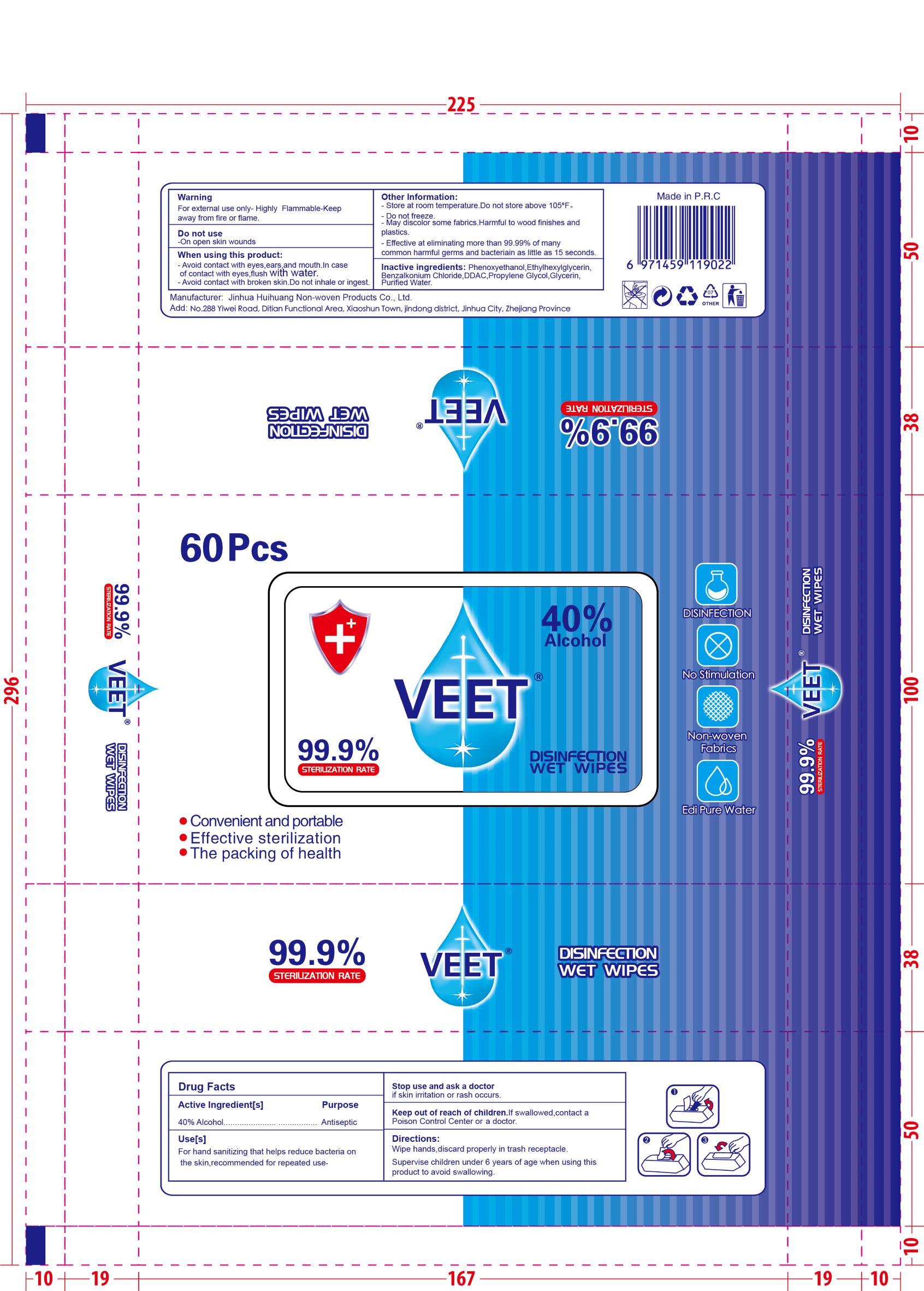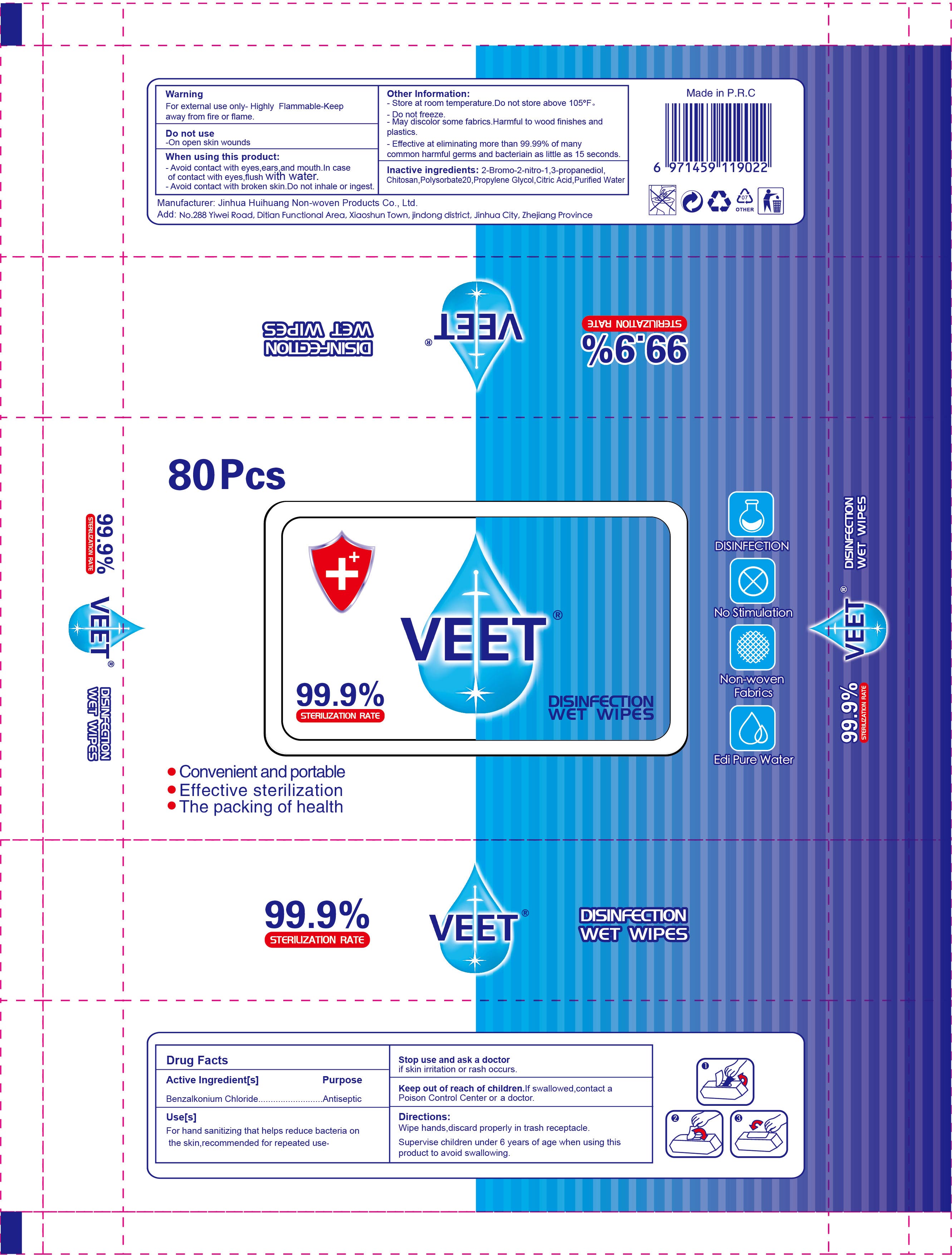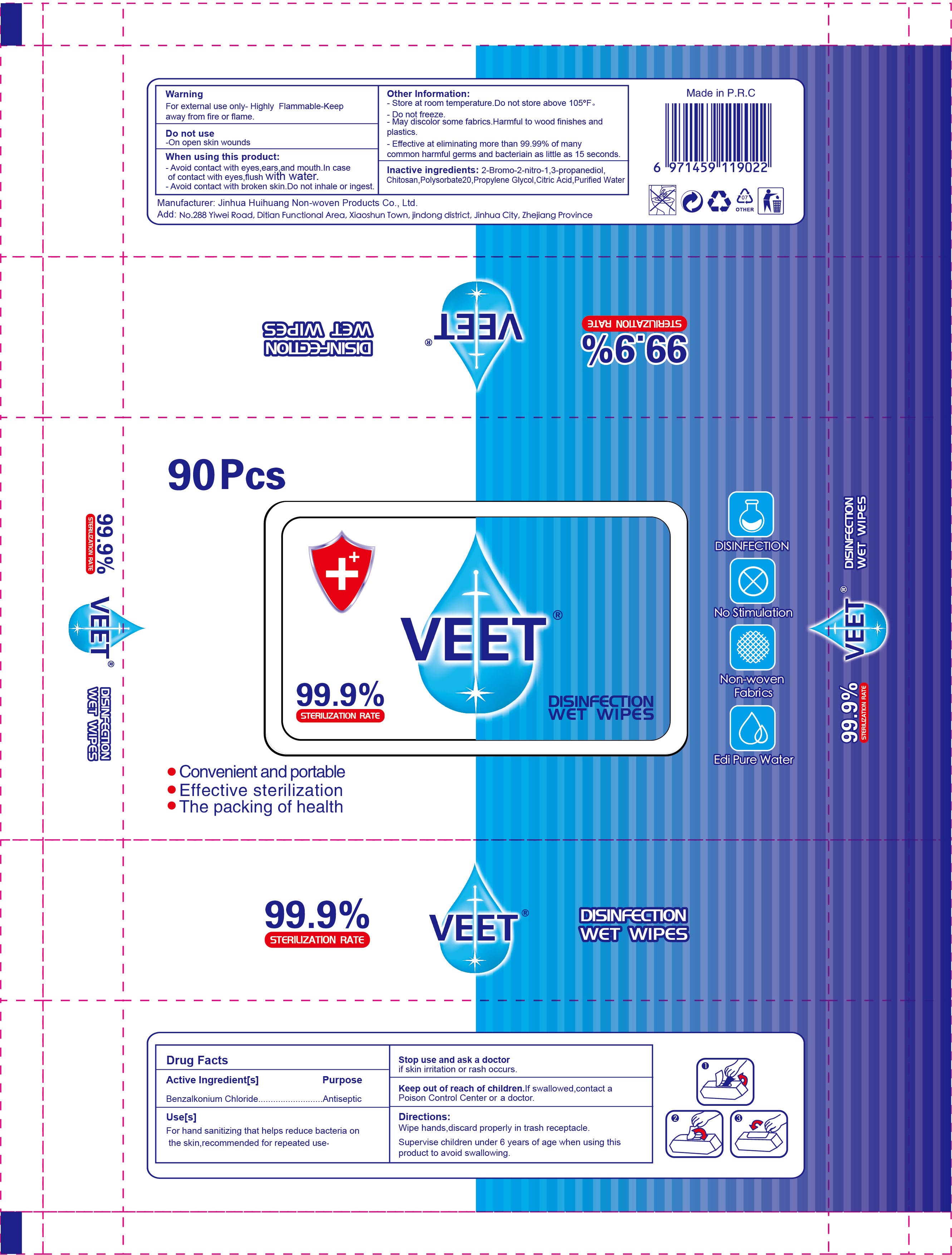 DRUG LABEL: veet disinfection wipes
NDC: 54016-003 | Form: CLOTH
Manufacturer: Jinhua Huihuang Non-woven Products Co., Ltd.
Category: otc | Type: HUMAN OTC DRUG LABEL
Date: 20200925

ACTIVE INGREDIENTS: ALCOHOL 40 mL/100 mL
INACTIVE INGREDIENTS: DIDECYLDIMONIUM CHLORIDE; GLYCERIN; PROPYLENE GLYCOL; WATER; BENZALKONIUM CHLORIDE; PHENOXYETHANOL; ETHYLHEXYLGLYCERIN

veet disinfection wipes
60pcs NDC: 54016-003-01

Active Ingredient(s)

40% Alcohol

Purpose

Antiseptic

Use

For hand sanitizing that helps reduce bacteria on the skin, recommended for repeated use.

Warnings

- For external use only.
- Highly Flammable - Keep away from fire or flame.

Do not use

- On open skin wounds.

WHEN USING

- Avoid contact with eyes, ears, and mouth. In case of contact with eyes, flush with water.
- Avoid contact with broken skin. Do not inhale or ingest.

Stop use and ask a doctor if skin irritation or rash occurs.

Keep out of reach of children. If swallowed, contact a Poison Control Center or a doctor.

Directions

- Wipe hands, discard properly in trash receptacle.
- Supervise children under 6 years of age when using this product to avoid swallowing.

Other information

- Store at room temperature. Do not store above 105℉.
- Do not freeze
- May discolor some fabrics. Harmful to wood finishes and plastics.
- Effective at eliminating more than 99.99% of many common harmful germs and bacteriain as little as 15 seconds.

Inactive ingredients

Phenoxyethanol, Ethylhexylglycerin, Benzalkonium Chloride, DDAC, Propylene Glycol, Glycerin, Purified Water.

Package Label - Principal Display Panel

60pcs NDC: 54016-003-01

1pcs NDC: 54016-003-02

10pcs NDC: 54016-003-03

15pcs NDC: 54016-003-04

20pcs NDC: 54016-003-05

25pcs NDC: 54016-003-06

30pcs NDC: 54016-003-07

40pcs NDC: 54016-003-08

50pcs NDC: 54016-003-09

80pcs NDC: 54016-003-10

90pcs NDC: 54016-003-11

100pcs NDC: 54016-003-12

120pcs NDC: 54016-003-13

150pcs NDC: 54016-003-14